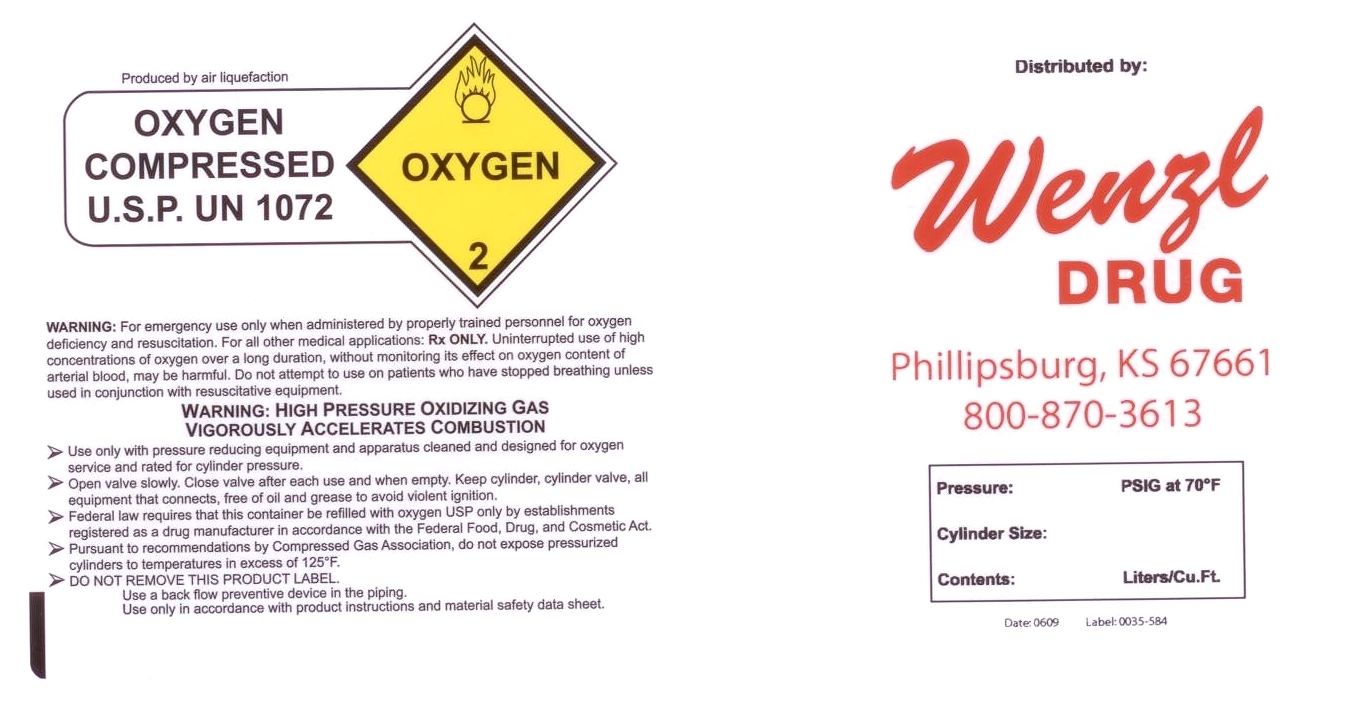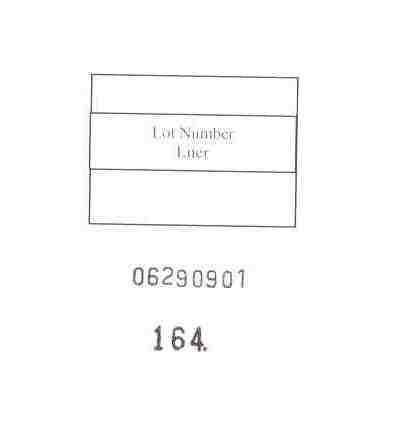 DRUG LABEL: OXYGEN
NDC: 49647-0001 | Form: GAS
Manufacturer: Wenzl Drug, Inc
Category: prescription | Type: HUMAN PRESCRIPTION DRUG LABEL
Date: 20090629

ACTIVE INGREDIENTS: OXYGEN 99 L/100 L

OXYGEN